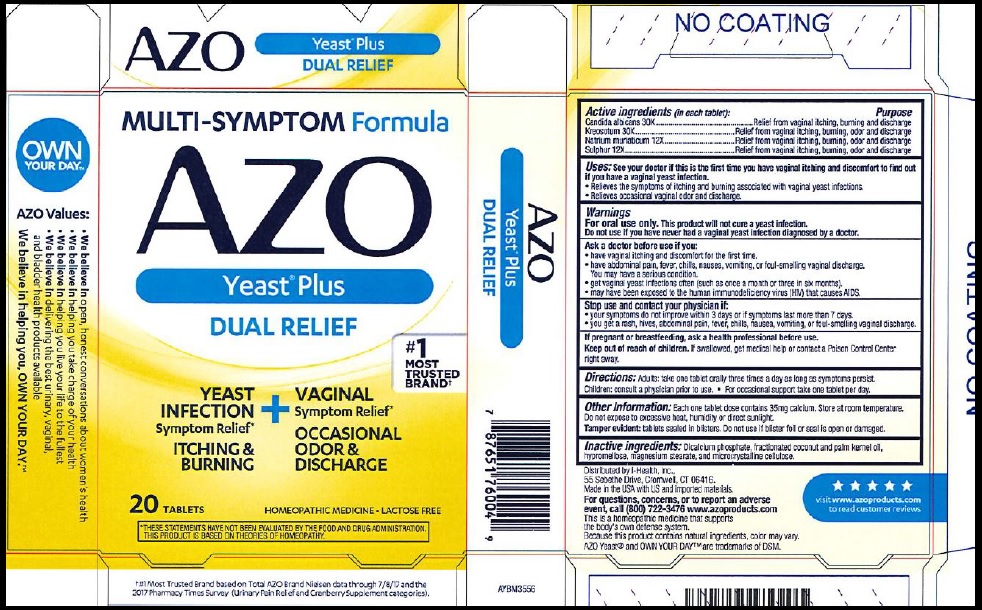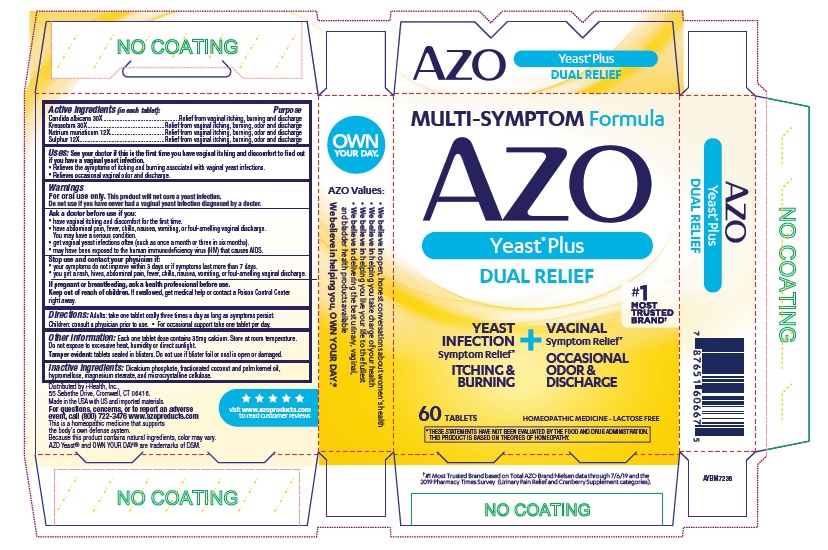 DRUG LABEL: AZO
NDC: 49973-667 | Form: TABLET
Manufacturer: i-Health, Inc.
Category: homeopathic | Type: HUMAN OTC DRUG LABEL
Date: 20251107

ACTIVE INGREDIENTS: CANDIDA ALBICANS 30 [hp_X]/1 1; WOOD CREOSOTE 30 [hp_X]/1 1; SODIUM CHLORIDE 12 [hp_X]/1 1; SULFUR 12 [hp_X]/1 1
INACTIVE INGREDIENTS: CALCIUM PHOSPHATE, DIBASIC, DIHYDRATE; CELLULOSE, MICROCRYSTALLINE; MAGNESIUM STEARATE; HYPROMELLOSES; MEDIUM-CHAIN TRIGLYCERIDES

AZO Yeast Plus

Active Ingredients (in each tablet):

Candida albicans30X

Kreosotum30X

Natrium muriaticum12X

Sulphur12X

Purpose

Relief from vaginal itching, burning and discharge

Relief from vaginal itching, burning, odor and discharge

Relief from vaginal itching, burning, odor and discharge

Relief from vaginal itching, burning, odor and discharge

Use:

See your doctor if this is the first time you have vaginal itching and discomfort to find out if you have a vaginal yeast infection.

- Relieves the symptoms of itching and burning associated with vaginal yeast infections.
- Relieves occasional vaginal odor and discharge.

Warnings:

For oral use only. This product will not cure a yeast infection.

Do not use if you have never had a vaginal yeast infection diagnosed by a doctor.

Ask a doctor before use if you

- have vaginal itching and discomfort for the first time.
- have abdominal pain, fever, chills, nausea, vomiting, or foul-smelling vaginal discharge. You may have a serious condition.
- get vaginal yeast infections often (such as once a month or three in six months).
- may have been exposed to human immunodeficiency virus (HIV) that causes AIDS.

Stop use and contact your physician if

- your symptoms do not improve within 3 days or if symptoms last more than 7 days.
- you get a rash, hives, abdominal pain, fever, chills, nausea, vomiting, or foul-smelling vaginal discharge.

PREGNANCY OR BREAST FEEDING

If pregnant or breastfeeding,ask a health professional before use.

Keep out of reach of children.If swallowed, get medical help or contact a Poison Control Center right away.

DOSAGE AND ADMINISTRATION

Directions: Adults: take one tablet orally three times a day as long as symptoms persist. Children: consult a physician prior to use.

- For occasional support take one tablet per day.

Other Information: Each one tablet dose contains 35 mg calcium. Store at room temperature. Do not expose to excessive heat, humidity or direct sunlight.

- Tamper evident: tablets sealed in blisters. Do not use if blister foil or seal is open or damaged.

INACTIVE INGREDIENT

Inactive Ingredients: Dicalcium phosphate, fractionated cocunut and palm kernel oil, hypromellose, magnesium stearate, and microcrystalline cellulose.

GENERAL PRECAUTIONS

This is a homeopathic medicine that supports the body's own defense system. Because this product contains natural ingredients, color may vary.

QUESTIONS

For questions, concerns, or to report an adverse event, call (800) 722-3476

www.azoproducts.com

Distributed by i-Health, Inc.

55 Sebethe Drive,

Cromwell, CT 06416

Made in the USA with US and imported materials.

PACKAGE LABEL

AZO

Yeast Plus

Yeast Infection Symptom Relief:*

ITCHING

BURNING

Vaginal Symptom Relief:*

OCCASIONAL ODOR &

DISCHARGE

#1 MOST TRUSTED BRAND

___ Tablets

Homeopathic Medicine Lactose Free

* THESE STATEMENTS HAVE NOT BEEN EVALUATED BY THE FOOD AND DRUG ADMINISTRATION